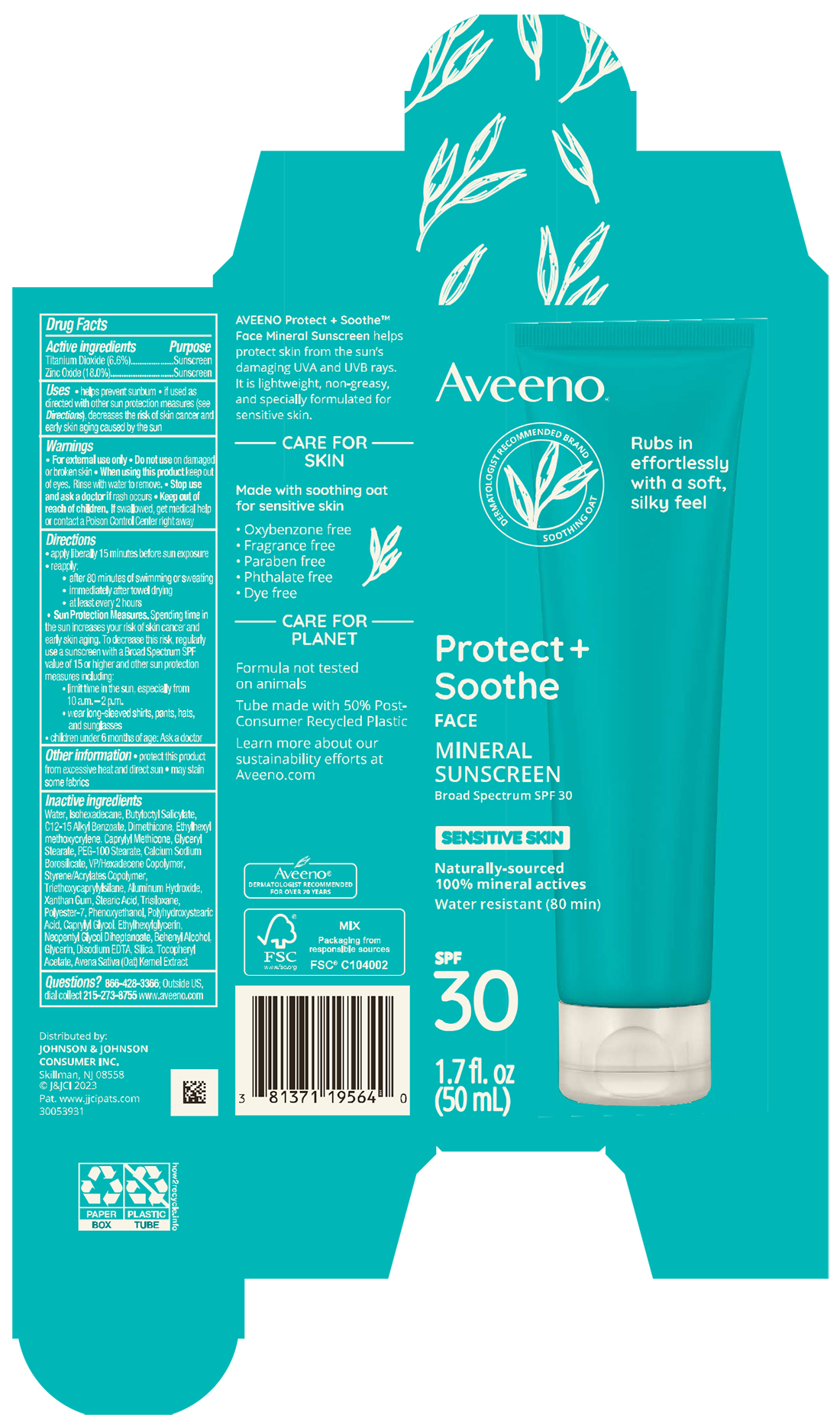 DRUG LABEL: Aveeno Protect Plus Soothe Face Mineral Sunscreen SPF 30
NDC: 69968-0786 | Form: LOTION
Manufacturer: Kenvue Brands LLC
Category: otc | Type: HUMAN OTC DRUG LABEL
Date: 20250604

ACTIVE INGREDIENTS: TITANIUM DIOXIDE 66 mg/1 mL; ZINC OXIDE 180 mg/1 mL
INACTIVE INGREDIENTS: STEARIC ACID; SILICON DIOXIDE; ETHYLHEXYL METHOXYCRYLENE; DIMETHICONE; TRISILOXANE; NEOPENTYL GLYCOL DIHEPTANOATE; WATER; ISOHEXADECANE; PEG-100 STEARATE; DOCOSANOL; CALCIUM SODIUM BOROSILICATE; ALUMINUM HYDROXIDE; OAT; EDETATE DISODIUM ANHYDROUS; BUTYL METHACRYLATE/METHYL METHACRYLATE/METHACRYLIC ACID/STYRENE CROSSPOLYMER; POLYESTER-7; PHENOXYETHANOL; GLYCERIN; .ALPHA.-TOCOPHEROL ACETATE; ALKYL (C12-15) BENZOATE; CAPRYLYL TRISILOXANE; GLYCERYL MONOSTEARATE; XANTHAN GUM; CAPRYLYL GLYCOL; ETHYLHEXYLGLYCERIN; BUTYLOCTYL SALICYLATE; VINYLPYRROLIDONE/HEXADECENE COPOLYMER; TRIETHOXYCAPRYLYLSILANE

Aveeno Protect Plus Soothe Face Mineral Sunscreen SPF 30

Drug Facts

ACTIVE INGREDIENT

Active ingredients | Purpose
Titanium Dioxide (6.6%) | Sunscreen
Zinc Oxide (18%) | Sunscreen

Uses

- helps prevent sunburn
- if used as directed with other sun protection measures (see Directions), decreases the risk of skin cancer and early skin aging caused by the sun

Warnings

For external use only

Do not use on damaged or broken skin

When using this product

keep out of eyes. Rinse with water to remove.

Stop use and ask a doctor if rash occurs

Keep out of reach of children. If swallowed, get medical help or contact a Poison Control Center right away

Directions

- apply liberally 15 minutes before sun exposure
- reapply:
  - after 80 minutes of swimming or sweating
  - immediately after towel drying
  - at least every 2 hours

- Sun Protection Measures. Spending time in the sun increases your risk of skin cancer and early skin aging. To decrease this risk, regularly use a sunscreen with a Broad-Spectrum SPF value of 15 or higher and other sun protection measures including:
- limit time in the sun, especially from 10 a.m. – 2 p.m.
- wear long-sleeved shirts, pants, hats, and sunglasses
- children under 6 months of age: Ask a doctor

Other information

- protect this product from excessive heat and direct sun
- may stain some fabrics

Inactive ingredients

Water, Isohexadecane, Butyloctyl Salicylate, C12-15 Alkyl Benzoate, Dimethicone, Ethylhexyl methoxycrylene, Caprylyl Methicone, Glyceryl Stearate, PEG-100 Stearate, Calcium Sodium Borosilicate, VP/Hexadecene Copolymer, Styrene/Acrylates Copolymer, Triethoxycaprylylsilane, Aluminum Hydroxide, Xanthan Gum, Stearic Acid, Trisiloxane, Polyester-7, Phenoxyethanol, Polyhydroxystearic Acid, Caprylyl Glycol, Ethylhexylglycerin, Neopentyl Glycol Diheptanoate, Behenyl Alcohol, Glycerin, Disodium EDTA, Silica, Tocopheryl Acetate, Avena Sativa (Oat) Kernel Extract

Questions?

866-428-3366; Outside US, dial collect 215-273-8755 www.aveeno.com

Distributed by:
JOHNSON & JOHNSON CONSUMER INC.
Skillman, NJ 08558

PRINCIPAL DISPLAY PANEL - 50mL Carton Label

Aveeno®

DERMATOLOGIST RECOMMENDED BRAND

SOOTHING OAT

Rubs in

effortlessly

With a soft,

Silky feel

Protect +

Soothe

FACE

MINERAL

SUNSCREEN

Broad Spectrum SPF 30

SENSITIVE SKIN

Naturally-sourced

100% mineral actives

Water resistant (80 min)

SPF

30

1.7 fl. oz

(50 mL)